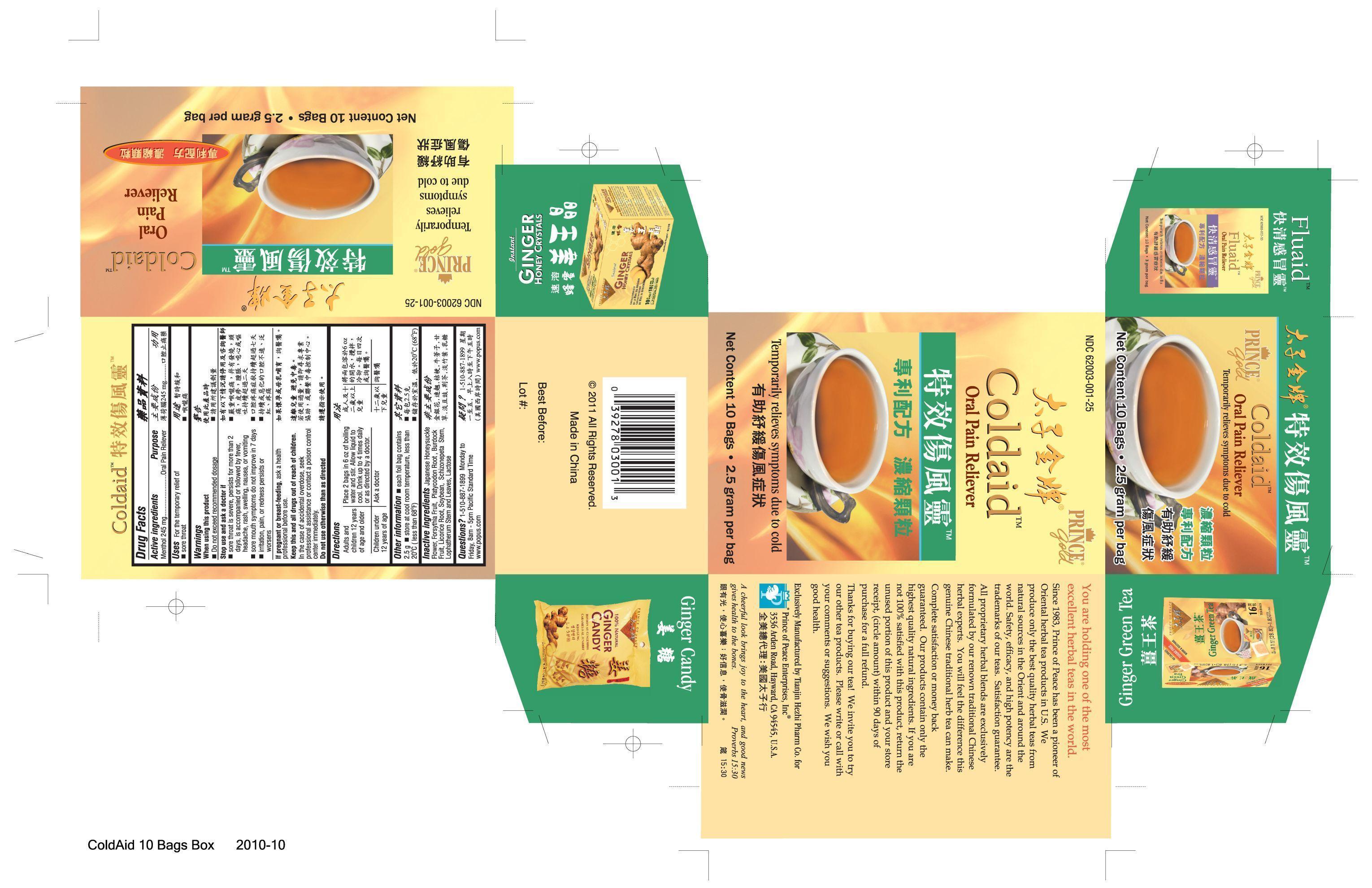 DRUG LABEL: Coldaid
NDC: 62003-001 | Form: GRANULE, FOR SOLUTION
Manufacturer: PRINCE OF PEACE ENTERPRISES INC.
Category: otc | Type: HUMAN OTC DRUG LABEL
Date: 20140401

ACTIVE INGREDIENTS: Menthol 490 mg/5 g
INACTIVE INGREDIENTS: LONICERA CAPRIFOLIUM FLOWER; FORSYTHIA SUSPENSA FRUIT; PLATYCODON GRANDIFLORUM LEAF; ARCTIUM LAPPA FRUIT; GLYCYRRHIZA GLABRA; SOYBEAN; SCHIZONEPETA TENUFOLIA SPIKE; LOPHATHERUM GRACILE LEAF; LACTOSE

Drug Facts

Active ingredients Purpose

Menthol 245 mg...........................Oral Pain Reliever

PURPOSE

Uses For the temporary relief of sore throat

When using this product

- Do not exceed recommended dosage

Stop use and ask a doctor if

- sore throat is severe, persists for more than 2 days, is accompanied or followed by fever, headache, rash, swelling, nausea, or vomiting
- sore mouth symptoms do not improve in 7 days
- irritation, pain, or redness persists or worsens

PREGNANCY OR BREAST FEEDING

If pregnant or breast-feeding, ask a health professional before use.

KEEP OUT OF REACH OF CHILDREN

Keep this and all drugs out of reach of children.

QUESTIONS

- Questions? 1-510-887-1899 Monday to Friday, 8 am - 5 pm Pacific Standard Time

- www.popus.com

Directions

Adults and children 12 years of age and older | Place 2 bags in 6 oz of boiling water and stir. Allow liquid to cool. Drink up to 4 times daily or as directed by a doctor.
Children under 12 years of age | Ask a doctor

WARNINGS

In the case of accidental overdose, seek professional assistance or contact a poison control center immediately.

Do not use otherwise than as directed.

INDICATIONS AND USAGE

Uses For the temporary relief of sore throat.

INACTIVE INGREDIENT

Japanese Hondysuckle Flower, Forsythia Fruit, Platycodon Root, Burdock Fruit, Licorice Root, Soybean, Schizonepeta Stem, Lophatherum Stem and Leaves, Lactose